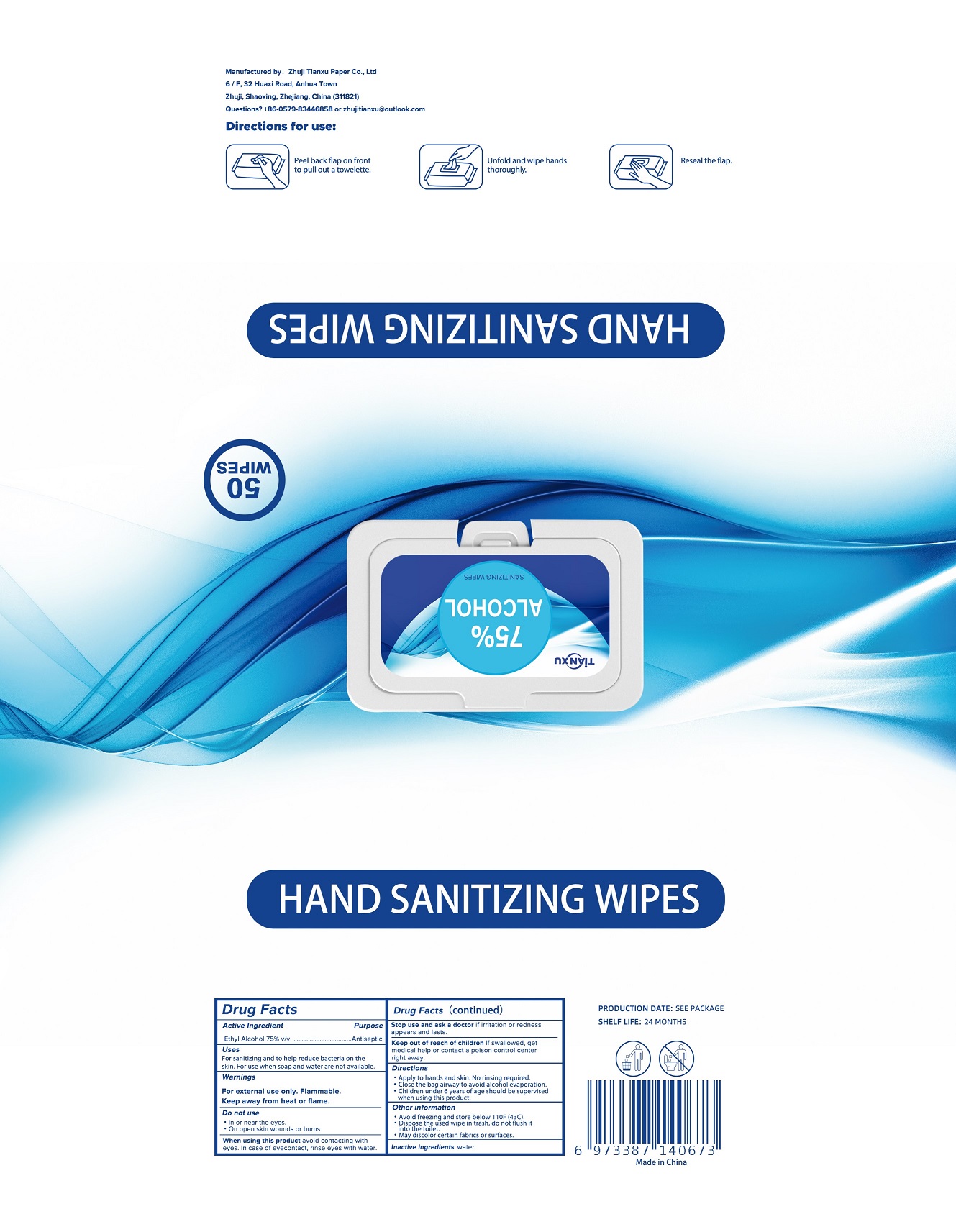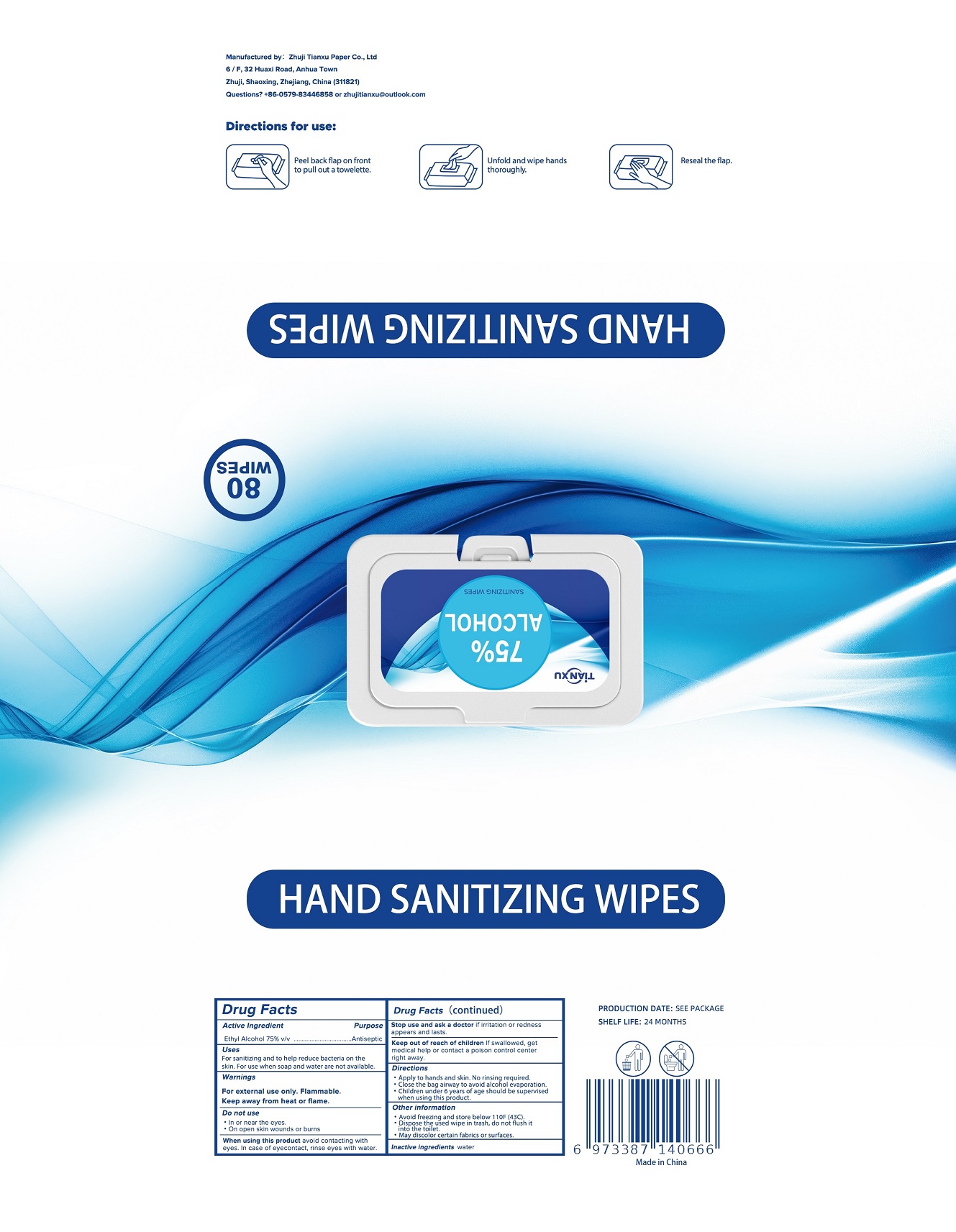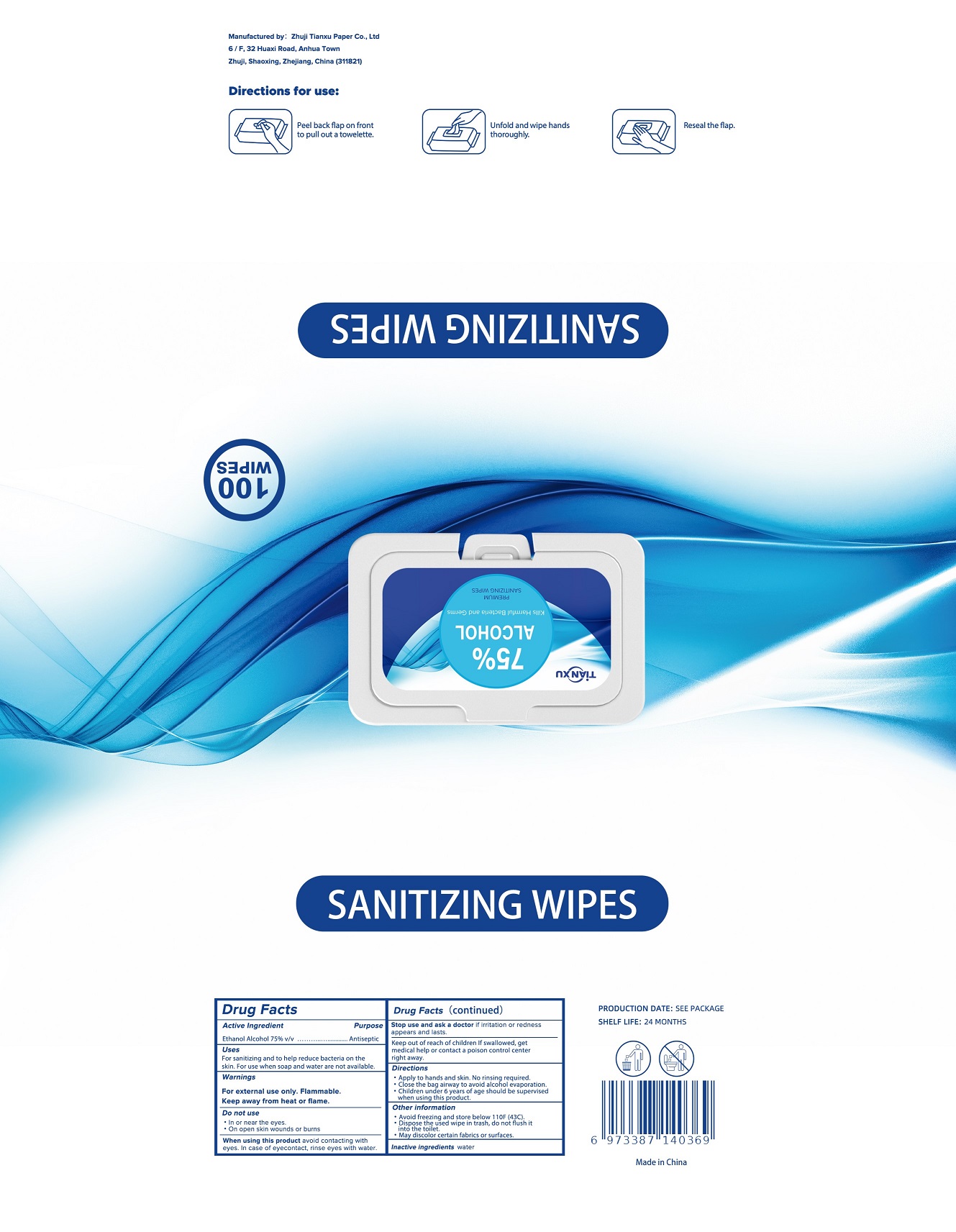 DRUG LABEL: ALCOHOL WIPES
NDC: 81147-101 | Form: CLOTH
Manufacturer: Zhuji Tianxu Paper Co., Ltd
Category: otc | Type: HUMAN OTC DRUG LABEL
Date: 20201125

ACTIVE INGREDIENTS: ALCOHOL 3 mL/1 1
INACTIVE INGREDIENTS: WATER

TianXu, Alcohol Wipes, Ethyl Alcohol 75% v/v

Active Ingredient

Ethyl Alcohol 75% v/v. Purpose: Antiseptic

Purpose

Antiseptic

Uses

For sanitizing and to help reduce bacteria on the skin. For use when soap and water are not available.

Warnings

For external use only. Flammable.

Keep away from heat or flame.

Do not use

- In or near eyes
- On open skin wounds or burns

When using this product avoid contacting with eyes. In case of eyecontact, rinse eyes with water.

Stop use and ask a doctor if irritation or redness appears and lasts.

Keep out of reach of children. If swallowed, get medical help or contact a poison control center right away.

Directions

- Apply to hands and skin. No rinsing required.
- Close the bag airway to avoid alcohol evaporation.
- Children under 6 years of age should be supervised when using this product.

Other information

- Avoid freezing and store below 110F (43C).
- Dispose the used wipe in trash, do not flush it into the toilet.
- May discolor certain fabrics or surface.

Inactive Ingredients

water